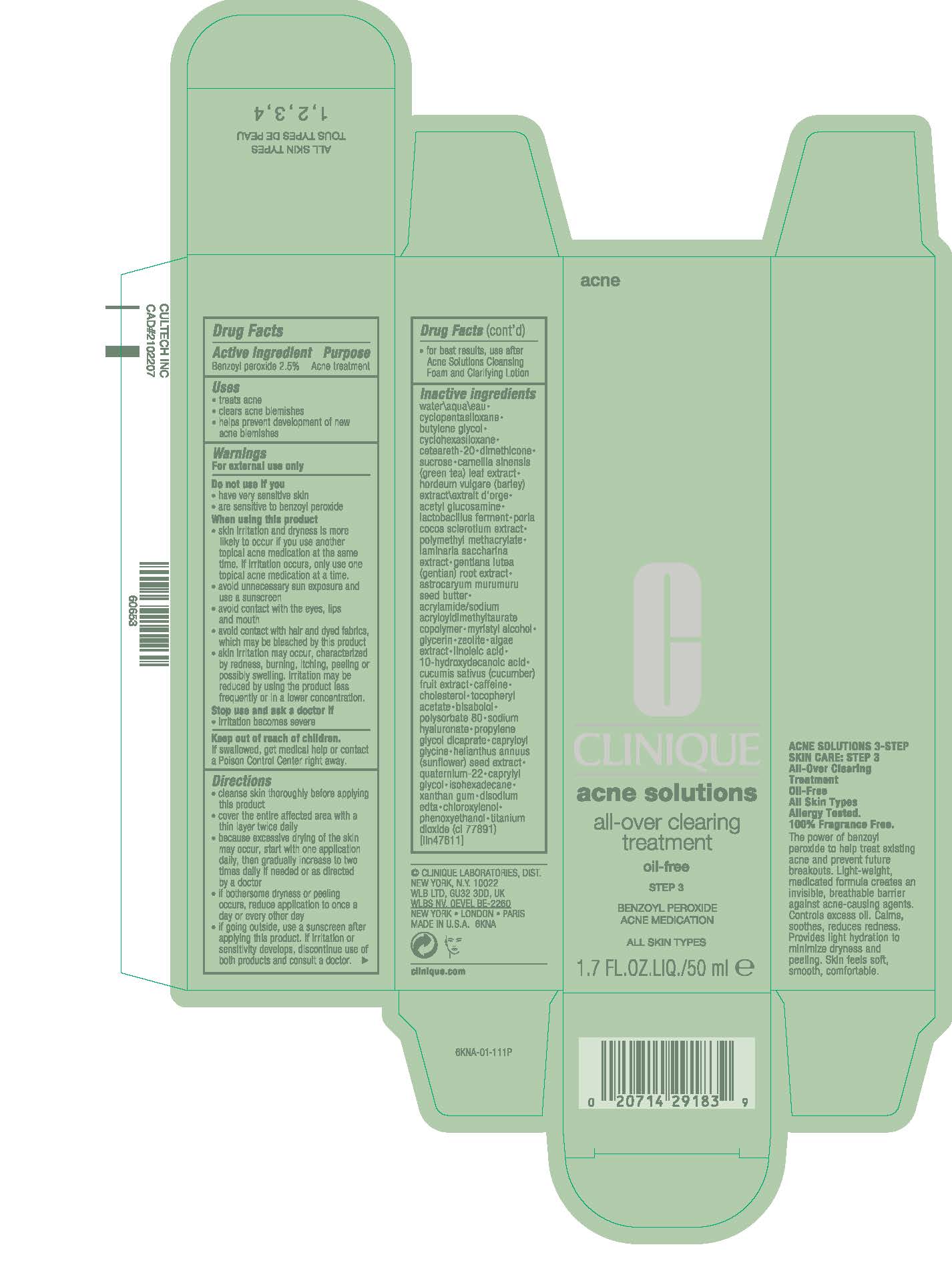 DRUG LABEL: ACNE SOLUTIONS
NDC: 49527-117 | Form: LOTION
Manufacturer: CLINIQUE LABORATORIES LLC
Category: otc | Type: HUMAN OTC DRUG LABEL
Date: 20250815

ACTIVE INGREDIENTS: BENZOYL PEROXIDE 25 mg/1 mL
INACTIVE INGREDIENTS: BUTYLENE GLYCOL; DIMETHICONE; ASTROCARYUM MURUMURU SEED BUTTER; GLYCERIN; CHOLESTEROL; XANTHAN GUM; SUCROSE; BARLEY; GLUCOSAMINE; GENTIANA LUTEA ROOT; SACCHAROMYCES LYSATE; MYRISTYL ALCOHOL; LINOLEIC ACID; CUCUMBER; .ALPHA.-TOCOPHEROL ACETATE, DL-; HYALURONATE SODIUM; CAPRYLYL GLYCOL; EDETATE DISODIUM; PHENOXYETHANOL; WATER; CYCLOMETHICONE 5; CYCLOMETHICONE 6; POLYOXYL 20 CETOSTEARYL ETHER; GREEN TEA LEAF; LIMOSILACTOBACILLUS REUTERI; FU LING; POLY(METHYL METHACRYLATE; 450000 MW); ACRYLAMIDOPROPYLTRIMONIUM CHLORIDE/ACRYLAMIDE COPOLYMER (400 MPA.S); ZEOLITE A; AGAR, UNSPECIFIED; 10-HYDROXYDECANOIC ACID; CAFFEINE; .ALPHA.-BISABOLOL, (+)-; POLYSORBATE 80; PROPYLENE GLYCOL DICAPRATE; CAPRYLOYL GLYCINE; SUNFLOWER SEED; QUATERNIUM-22; ISOHEXADECANE; CHLOROXYLENOL; TITANIUM DIOXIDE

ACNE SOLUTIONS
ALL-OVER CLEARING TREATMENT

ACTIVE INGREDIENT: BENZOYL PEROXIDE 2.5%

Purpose

Acne Treatment

Directions

- CLEANS SKIN THOROUGHLY BEFORE APPLYING THIS PRODUCT
- COVER THE ENTIRE AFFECTED AREA WITH A THIN LAYER ONE TO THREE TIMES DAILY
- BECAUSE EXCESSIVE DRYING OF THE SKIN MAY OCCUR, START WITH ONE APPLICATION DAILY, THEN GRADUALLY INCREASE TO TWO OR THREE TIMES DAILY IF NEEDED OR AS DIRECTED BY A DOCTOR
- IF BOTHERSOME DRYNESS OR PEELING OCCURS, REDUCE APPLICATION TO ONCE A DOY OR EVERY OTHER DAY
- IF GOING OUTSIDE, USE A SUNSCREEN AFTER APPLYING THIS PRODUCT. IF IRRITATION OR SENSITIVITY DEVELOPS, DISCONTINUE USE OF BOTH PRODUCTS AND CONSULT A DOCTOR
- FOR BEST RESULTS, USE AFTER ACNE SOLUTIONS CLEANSING FOAM AND CLARIFYING LOTION

Uses

Treats Acne

Clears acne blemishes

Helps prevent development of new acne blemishes

WARNINGS

WARNING: FOR EXTERNAL USE ONLY

DO NOT USE IF YOU

- HAVE VERY SENSITIVE SKIN
- ARE SENSITIVE TO BENZOYL PEROXIDE

WHEN USING THIS PRODUCT

- SKIN IRRITATION AND DRYNESS IS MORE LIKELY TO OCCUR IF YOU USE ANOTHER TOPICAL ACNE MEDICATION AT THIS TIME. IF IRRITATION OCCURS, USE ONLY ONE TOPICAL ACNE MEDICATION AT AT TIME
- AVOID UNNECESSARY SUN EXPOSURE AND USE A SUNSCREEN
- AVOID CONTACT WITH THE EYES, LIPS, AND MOUTH
- AVOID CONTACT WITH HAIR AND DYED FABRICS, WHICH MAY BE BLEACHED BY THIS PRODUCT
- SKIN IRRITATION MAY OCCUR, CHARACTERIZED BY REDNESS, BURNING, ITCHING, PEELING OR POSSIBLY SWELLING. IRRITATION MAY BE REDUCED BY USING THE PRODUCT LESS FREQUENTLY OR IN A LOWER CONCENTRATION

STOP USE AND ASK A DOCTOR IF

- IRRITATION BECOMES SEVERE

KEEP OUT OF REACH OF CHILDREN

IF SWALLOWED, GET MECICAL HELP OR CONTACT A POISON CONTROL CENTER RIGHT AWAY.

Inactive ingredients

water\aqua\eau∙cyclopentasiloxane∙butylene glycol∙cyclohexasiloxane∙ceteareth-20∙dimethicone∙sucrose∙camellia sinensis (green tea) leaf extract∙hordeum vulgare (barley) extract\extrait d'orge∙acetyl glucosamine∙lactobacillus ferment∙poria cocos sclerotium extract∙polymethyl methacrylate∙laminaria saccharina extract∙gentiana lutea (gentian) root extract∙astrocaryum murumuru seed butter∙acrylamide/sodium acryloyldimethyltaurate copolymer∙myristyl alcohol∙glycerin∙zeolite∙algae extract∙linoleic acid∙10-hydroxydecanoic acid∙cucumis sativus (cucumber) fruit extract∙caffeine∙ cholesterol∙tocopheryl acetate∙bisabolol∙polysorbate 80∙sodium hyaluronate∙propylene glycol dicaprate∙capryloyl glycine∙helianthus annuus (sunflower) seed extract∙quaternium-22∙caprylyl glycol∙isohexadecane∙xanthan gum∙disodiumedta∙chloroxylenol∙phenoxyethanol∙titanium dioxide (ci 77891) [iln47611]

PRINCIPAL DISPLAY PANEL - 50 mL Tube Carton

CLINIQUE

acne solutions

all-over clearing
treatment

oil-free

STEP 3

BENZOYL PEROXIDE
ACNE MEDICATION

ALL SKIN TYPES

1.7 FL.OZ.LIQ./50 ml ℮